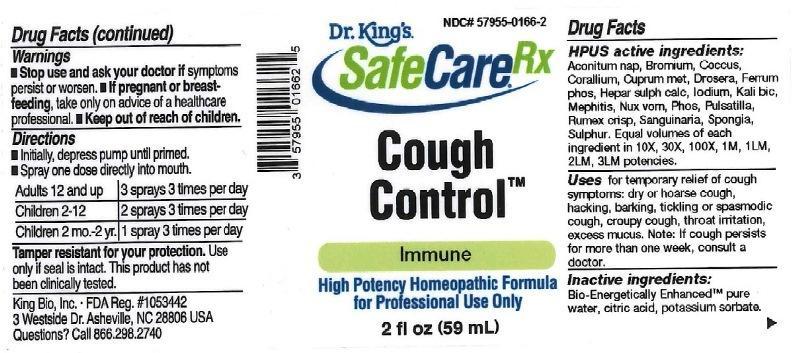 DRUG LABEL: Cough Control
NDC: 57955-0166 | Form: LIQUID
Manufacturer: King Bio Inc.
Category: homeopathic | Type: HUMAN OTC DRUG LABEL
Date: 20161109

ACTIVE INGREDIENTS: ACONITUM NAPELLUS 10 [hp_X]/59 mL; BROMINE 10 [hp_X]/59 mL; PROTORTONIA CACTI 10 [hp_X]/59 mL; CORALLIUM RUBRUM EXOSKELETON 10 [hp_X]/59 mL; COPPER 10 [hp_X]/59 mL; DROSERA ROTUNDIFOLIA 10 [hp_X]/59 mL; FERROSOFERRIC PHOSPHATE 10 [hp_X]/59 mL; CALCIUM SULFIDE 10 [hp_X]/59 mL; IODINE 10 [hp_X]/59 mL; POTASSIUM DICHROMATE 10 [hp_X]/59 mL; MEPHITIS MEPHITIS ANAL GLAND FLUID 10 [hp_X]/59 mL; STRYCHNOS NUX-VOMICA SEED 10 [hp_X]/59 mL; PHOSPHORUS 10 [hp_X]/59 mL; PULSATILLA VULGARIS 10 [hp_X]/59 mL; RUMEX CRISPUS ROOT 10 [hp_X]/59 mL; SANGUINARIA CANADENSIS ROOT 10 [hp_X]/59 mL; SPONGIA OFFICINALIS SKELETON, ROASTED 10 [hp_X]/59 mL; SULFUR 10 [hp_X]/59 mL
INACTIVE INGREDIENTS: WATER; ANHYDROUS CITRIC ACID; POTASSIUM SORBATE

Cough Control

ACTIVE INGREDIENT

Drug Facts__________________________________________________________________________________________________________

HPUS active ingredients: Aconitum napellus, Bromium, Coccus cacti, Corallium rubrum, Cuprum metallicum, Drosera rotundifolia, Ferrum phosphoricum, Hepar sulphuris calcareum, Iodium, Kali bichromicum, Mephitis mephitica, Nux vomica, Phosphorus, Pulsatilla, Rumex crispus, Sanguinaria canadensis, Spongia tosta, Sulphur. Equal volumes of each ingredient in 10X, 30X, 100X, 1M, 1LM, 2LM, 3LM potencies.

INDICATIONS AND USAGE

Uses for temporary relief of cough symptoms: dry or hoarse cough, hacking, barking, tickling or spasmodic cough, croupy cough, throat irritation, excess mucus. Note: If cough persists for more than one week, consult a doctor.

INACTIVE INGREDIENT

Inactive Ingredients: Bio-Energetically Enhanced™ pure water, citric acid and potassium sorbate.

Warnings

- Stop use and ask your doctor if symptoms persist or worsen.
- If pregnant or breast-feeding, take only on advice of a healthcare professional.

- Keep out of reach of children.

Directions

- Initially, depress pump until primed.
- Spray one dose directly into mouth.
- Adults: 3 sprays 3 times per day.
- Children: 2-12: 2 sprays 3 times per day.
- Use additionally as needed, up to 6 times per day.

OTHER SAFETY INFORMATION

Tamper resistant for your protection. Use only if safety seal is intact. This product has not been clinically tested.

PURPOSE

Uses: for temporary relief of cough symptoms:

- dry or hoarse cough
- hacking, barking, tickling or spasmodic cough
- croupy cough
- throat irritation
- excess mucus
- Note: If cough persists for more than one week, consult a doctor.